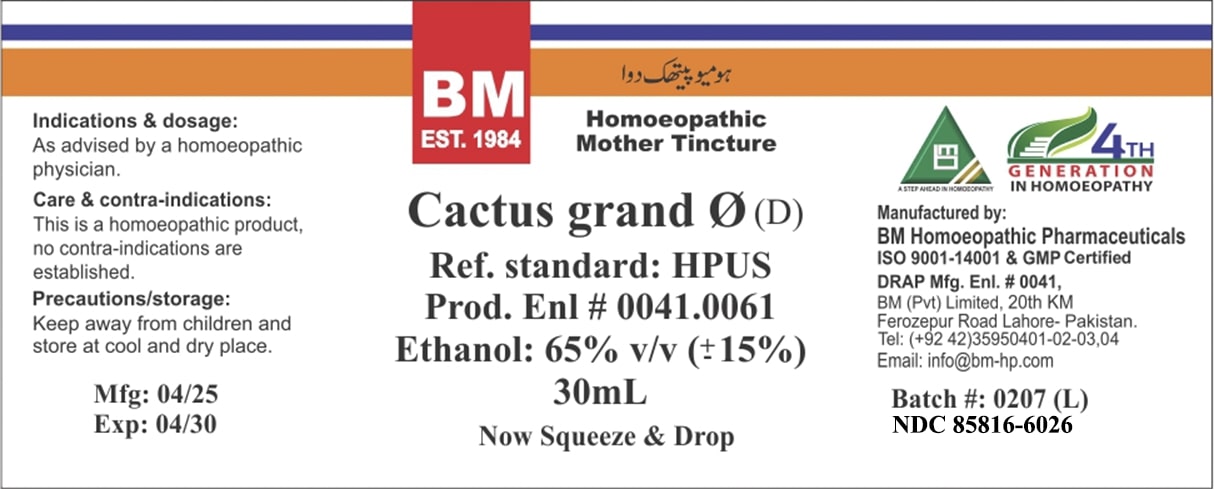 DRUG LABEL: BM Cactus Grandiflorus
NDC: 85816-6026 | Form: TINCTURE
Manufacturer: BM Private Limited
Category: homeopathic | Type: HUMAN OTC DRUG LABEL
Date: 20250627

ACTIVE INGREDIENTS: SELENICEREUS GRANDIFLORUS STEM 3 [hp_X]/1 mL
INACTIVE INGREDIENTS: WATER 0.315 mL/1 mL; ALCOHOL 0.684 mL/1 mL

BM Cactus Grandiflorus tincture

Indications & dosage: As advised by a homoeopathic physician.

PURPOSE

Indications & dosage: As advised by a homoeopathic physician.

Indications & dosage: As advised by a homoeopathic physician.

CONTRAINDICATIONS

Care & contra-indications: This is a homoeopathic product, no contra-indications are established.

KEEP OUT OF REACH OF CHILDREN

Precautions/storage: Keep away from children and store at cool and dry place.

WARNINGS

Precautions/storage: Keep away from children and store at cool and dry place.

STORAGE AND HANDLING

Precautions/storage: Keep away from children and store at cool and dry place.

ACTIVE INGREDIENT

Cactus Grandiflorus

INACTIVE INGREDIENT

purified water and alcohol

Entire package label